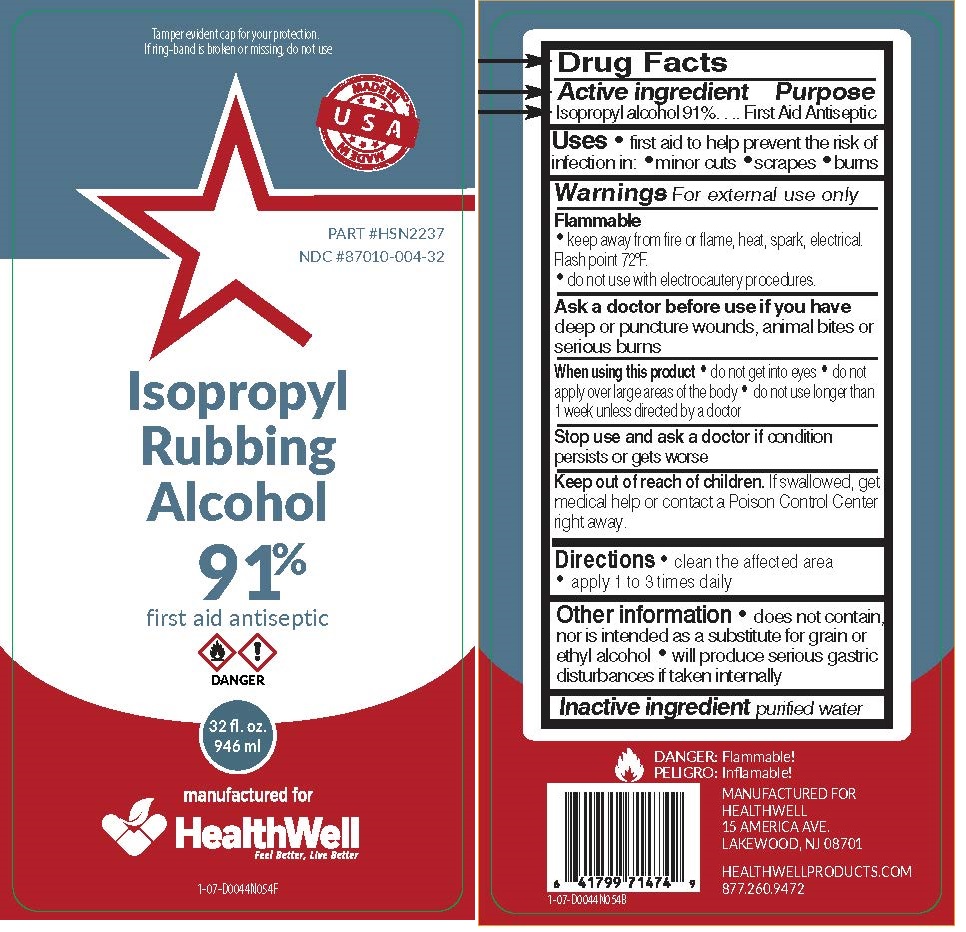 DRUG LABEL: Isopropyl Rubbing Alcohol
NDC: 87010-004 | Form: SOLUTION
Manufacturer: Healthwell
Category: otc | Type: HUMAN OTC DRUG LABEL
Date: 20201007

ACTIVE INGREDIENTS: ISOPROPYL ALCOHOL 91 mL/100 mL
INACTIVE INGREDIENTS: WATER

Isopropyl Alcohol 91%

Active Ingredient

Isopropyl Alcohol 91%

Purpose

First Aid Antiseptic

Uses

first aid to help prevent the risk of infection in: ● minor cuts ● scrapes ● burns

Warnings

For external use only

Flammable

Keep away from fire or flame, heat, spark, electrical

Do not use with electrocautery procedures

Ask a doctor before use if you have

deep or puncture wounds, animal bites or serious burns

When using this product

● do not get into eyes

● do ot apply over large areas of the body

● do not use longer than 1 week unless directed by a doctor

Stop use and ask a doctor if condition persists or gets worse

Keep out of reach of children.

If swallowed, get medical help or contact a Poison Control Center right away

Directions

● clean the affected area

● apply a small amount of this product 1 to 3 times daily

Other Information

does not contain, nor is intended as a substitute for grain or ethyl alcohol

Will produce serious gastric disturbances if taken internally

Inactive Ingredient

purified water

PACKAGE LABEL

TAMPER EVIDENT CAP FOR YOUR PROTECTION. IF RING-BAND IS DETACHED FROM CAP OR MISSING DO NOT USE.

Part # HSN2237

NDC #87010-004-32

Isopropyl Rubbing Alcohol 91%

FIRST AID ANTISEPTIC

Manufactured for Healthwell

32 FL OZ

(946 mL)